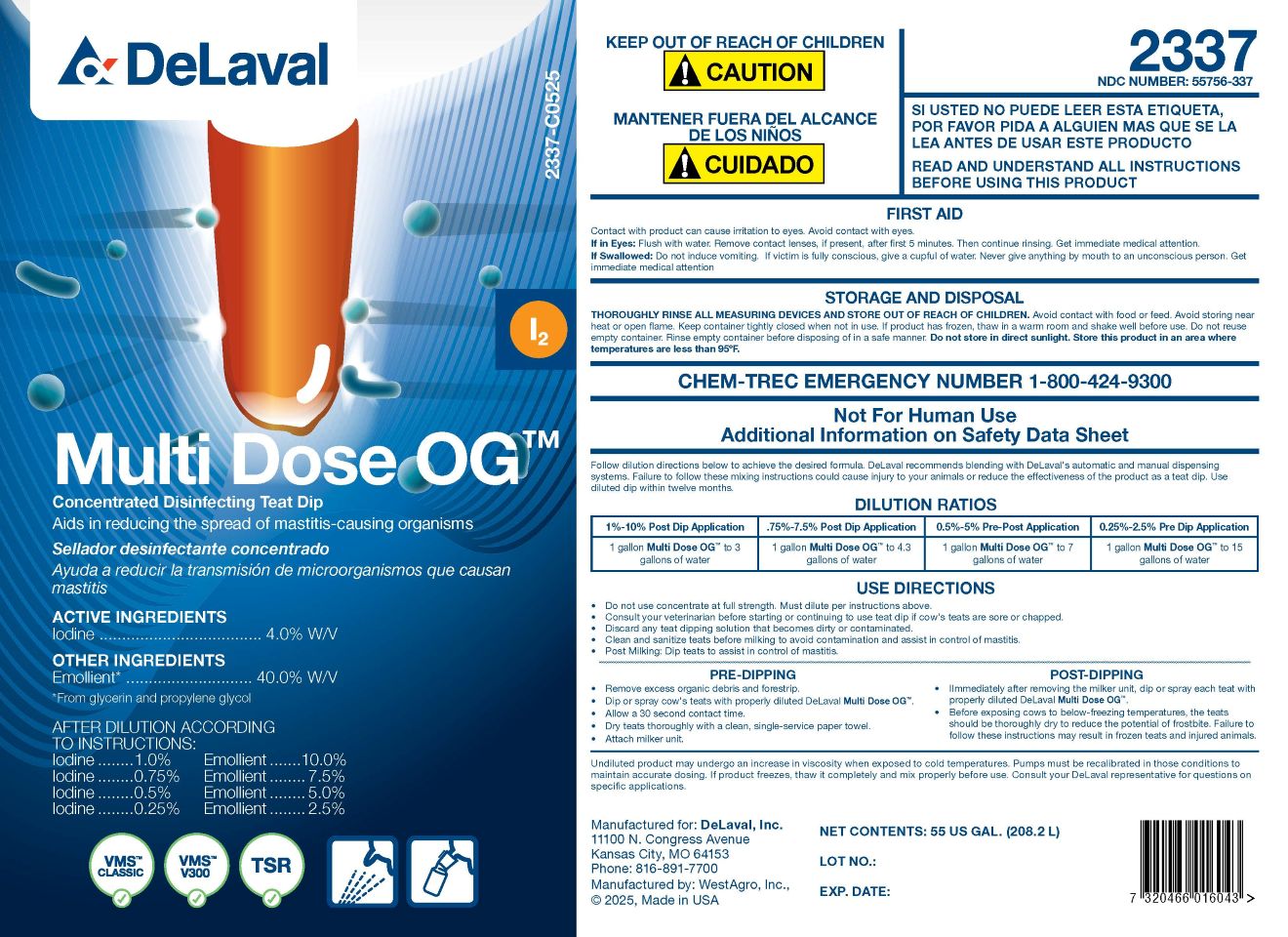 DRUG LABEL: Multi Dose OG
NDC: 55756-337 | Form: SOLUTION, CONCENTRATE
Manufacturer: DeLaval
Category: animal | Type: OTC ANIMAL DRUG LABEL
Date: 20260125

ACTIVE INGREDIENTS: IODINE 4000 mg/1 L
INACTIVE INGREDIENTS: WATER; ANHYDROUS CITRIC ACID; C9-11 PARETH-8; POLOXAMER 335; PROPYLENE GLYCOL; GLYCERIN; SODIUM HYDROXIDE

Multi Dose OG™

Multi Dose OG™

Concentrated Iodine Teat Sanitizer

Adis in reducing the spread of mastitis-causing organisms

ACTIVE INGREDIENTS

Iodine .................................. 4.0% W/V

Emollient (contains glyerin) ....40.0% W/V

AFTER DILUTION ACCORDING TO INSTRUCTIONS

Iodine........1.0% Emollient........10.0%

Iodine........0.75% Emollient..........7.5%

Iodine........0.5% Emollient..........5.0%

Iodine........o.25% Emollient..........2.5%

KEEP OUT OF REACH OF CHILDREN

! CAUTION

PRECAUTIONS

READ AND UNDERSTAND ALL INSTRUCTIONS BEFORE USING THIS PRODUCT

Contact with product can cause irritation to eyes. Avoid contact with eyes.

Eye Contact: Flush with water. Remove contact lenses, if present, after first 5 minutes. Then continue rinsing. Get immediate medical attention.

If Swallowed: Do not induce vomiting. If victim is fully conscious, give a cupful of water. Never give anything by mouth to an unconscious person. Get immediate medical attention.

STORAGE AND DISPOSAL

THOROUGHLY RINSE ALL MEASURING DEVICES AND STORE OUT OF REACH OF CHILDREN. Avoid contact with food or feed. Avoid storing near heat or open flame. Keep container tightly closed when not in use. If product has frozen, thaw in a warm room and shake well before use. Do not reuse empty container. Rinse empty container before disposing of in a safe manner. Do not store in direct sunlight. Store this product in an area where temperatures are less then 96°F.

CHEM-TREC EMERGENCY NUMBER 1-800-424-9399

Not for human use

Additional Information on Safety Data Sheet

DOSAGE AND ADMINISTRATION

Follow dilution directions below to achieve the desired formula. DeLaval recommends blending with DeLaval's automatic and manual dispersing systems. Failure to follow these mixing instructions could cause injury to your animals or reduce the effectiveness of the product as a teat dip. Use diluted dip within twelve months.

USE DIRECTIONS
1%-10% Post Dip Application | 0.75%-7.5% Post Dip Application | 0.5%-5.0% Pre-Post Application | 0.25%-2.5% Pre Dip Application
1 gallon DeLaval Multi Dose OG™ to 3 gallons of water | 1 gallon of DeLaval Multi Dose OG™ to 4.3 gallons of water | 1 gallon of DeLaval Multi Dose OG™ to 7 gallons of water | 1 gallon of DeLaval Multi Dose OG™ to 15 gallons of water

USE DIRECTIONS

- Do not use concentrate at full strength. Must dilute per instructions above.
- Consult your veterinarian before starting or continuing to use teat dip if cow's teats are sore or chapped.
- Discard any teat dipping solution that becomes dirty or contaminated.
- Clean and sanitize teat before milking to avoid contamination and assist in control of mastitis.
- Post Milking: Dip teats to assist in control of mastitis.

PRE-DIPPING

- Remove excess organic debris and forestrip.
- Dip or spray cow's teats with properly diluted DeLaval Multi Dose OG™.
- Allow a 30 second contact time.
- Dry teats thoroughly with a clean, single-service paper towel.
- Attach milker unit.

POST-DIPPING

- Immediately after removing the milker unit, dip or spray each teat with properly diluted DeLaval Multi Dose OG™.
- Before exposing cows to below-freezing temperatures, the teats should be thoroughly dry to reduce the potential of frostbite. Failure to follow these instructions may result in frozen teats and injured animals.